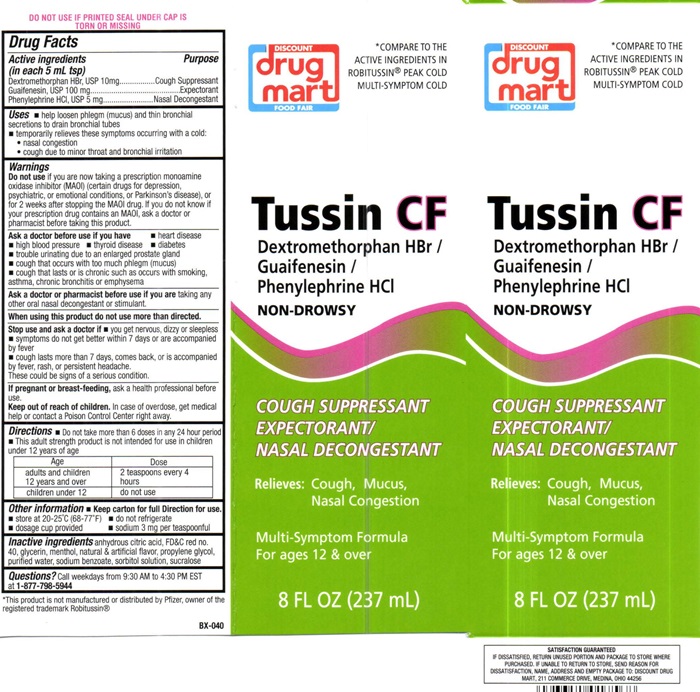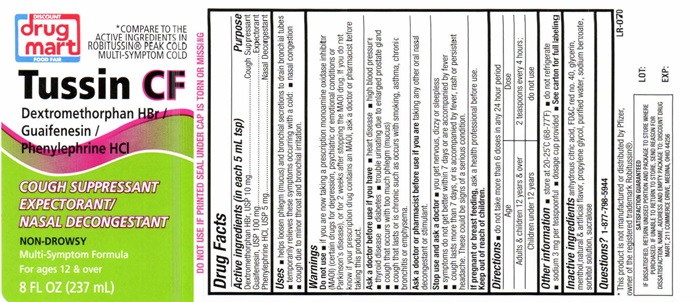 DRUG LABEL: Tussin CF
NDC: 53943-504 | Form: LIQUID
Manufacturer: Discount Drug Mart
Category: otc | Type: HUMAN OTC DRUG LABEL
Date: 20251223

ACTIVE INGREDIENTS: DEXTROMETHORPHAN HYDROBROMIDE 10 mg/5 mL; GUAIFENESIN 100 mg/5 mL; PHENYLEPHRINE HYDROCHLORIDE 5 mg/5 mL
INACTIVE INGREDIENTS: ANHYDROUS CITRIC ACID; FD&C RED NO. 40; GLYCERIN; MENTHOL; PROPYLENE GLYCOL; WATER; SODIUM BENZOATE; SORBITOL; SUCRALOSE

Drug Facts Active ingredients (in each 5 mL tsp)

Dextromethorphan HBr, USP 10 mg

Guaifenesin, USP 100 mg

Phenylephrine HCL, USP 5 mg

Purpose

Cough Suppressant

Expectorant

Naasal Decongestant

Keep out of reach of children. In case of overdose, get medical help or contact a Poison Control Center right away.

Uses

- help loosen phlegm (mucus) and thin bronchial secretions to drain bronchial tubes
- temporarily relieves these symptoms occuring with a cold:
- nasal congestion
- cough due to minor throat and bronchial irritation

Warnings

DO NOT USE IF PRINTED SEAL UNDER CAP IS TORN OR MISSING.

Do not use if you are now taking a prescription monoamine oxidase inhibitor (MAOI) (certain drugs for depression, psychiatric or emotional conditions or Parkinson's disease), or for 2 weeks after stopping the MAOI drug. If you do not know if your prescription drug contains an MAOI, ask a doctor or pharmacist before taking this product.

Ask a doctor before use if you have

- high blood pressure
- heart disease
- diabetes
- thyroid disease
- trouble urinating due to an enlarged prostate gland
- cough that occurs with too much phlegm (mucus)
- cough that lasts or is chronic such as occurs with smoking, asthma, chronic bronchitis or emphysema

Ask a doctor or pharmacist before use if you are

taking any other oral nasal decongestant or stimulant.

When using this product

do not use more than directed.

Stop use and ask a doctor if

- you get nervous, dizzy or sleepless
- symptoms do not get better within 7 days or are accompanied by fever
- cough lasts for more than 7 days, comes back, or is accompanied by fever, rash, or persistant headache.

These could be signs of a serious condition.

If pregnant or breast-feeding,

as a health professional before use.

Directions

- Do not take more than 6 doses in any 24 hour period
- This adult strength product is not intended for use in children under 12 years of age

Age | Dose
adults and children 12 years and over | 2 teaspoons every 4 hours
children under 12 | do not use

Other information

- Keep carton for full Directions for use.
- store at 20°-25°C (68°-77°F)
- do not refrigerate
- dosage cup provided
- sodium 3 mg per teaspoonful

Inactive ingredients

Anhydrous citric acid, FD and red # 40, glycerin, menthol, natural and artifical flavor, propylene glycol, purified water, sodium benzoate, sorbitol solution, sucralose

Questions?

Call weekdays from 9:30 AM to 4:30 PM EST at 1-877-798-5944

DISCOUNT drug mart FOOD FAIR Tussin CF product label

*COMPARE TO THE ACTIVE INGREDIENTS IN ROBITUSSIN® PEAK COLD COUGH MULTI-SYMPTOM COLD

DISCOUNT

drug mart

FOOD FAIR

Tussin CF

Dextromethorphan HBr/ Guaifenesin / Phenylephrine HCL

NON-DROWSY

COUGH SUPPRESSANT

EXPECTORANT

NASAL DECONGESTANT

Relieves: Cough, Mucus, Nasal Congestion

Multi-Symptom Formula

For ages 12 and over

8 FL OZ (237 mL)

* This product is not manufactured or distributed bynPfizer, owner of the registered trademark Robitussin®

BX-040 LOT: EXP:

SATISFACTION GUARANTEED
IF DISSASIFIED , RETURN UNUSED PORTION AND PACKAGE TO STORE WHERE PURCHASED. IF UNABLE TO RETURN TO STORE, SEND REASON FOR DISSATISFACTION, NAME, ADDRESS AND EMPTY PACKAGE TO: DISCOUNT DRUG MART, 211 COMMERCE DRIVE, MEDINA, OHIO 44256

res